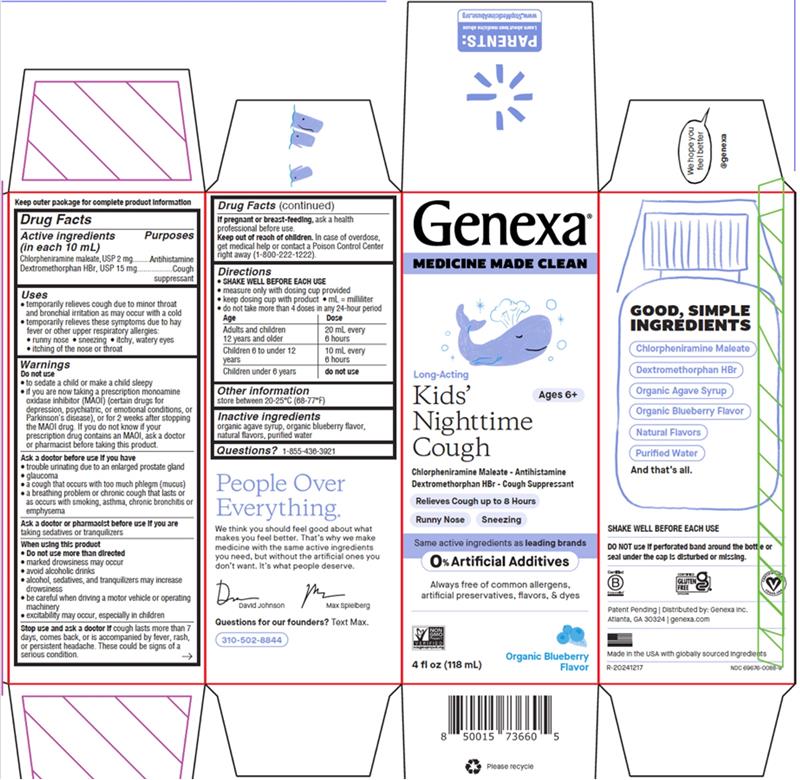 DRUG LABEL: Nighttime Cough-Kids
NDC: 69676-0088 | Form: SOLUTION
Manufacturer: Genexa
Category: otc | Type: HUMAN OTC DRUG LABEL
Date: 20250801

ACTIVE INGREDIENTS: DEXTROMETHORPHAN HYDROBROMIDE 15 mg/10 mL; CHLORPHENIRAMINE MALEATE 2 mg/10 mL
INACTIVE INGREDIENTS: AGAVE TEQUILANA STEM; WATER; BLUEBERRY

Kids' Nighttime Cough

Drug Facts

Active ingredients (in each 10 mL)

Chlorpheniramine maleate, USP 2 mg

Dextromethorphan HBr, USP 15 mg

Purposes

Antihistamine

Cough suppressant

Uses

• temporarily relieves cough due to minor throat and bronchial irritation as may occur with a cold

• temporarily relieves these symptoms due to hay fever or other upper respiratory allergies:

• runny nose • sneezing • itchy, watery eyes • itching of the nose or throat

Warnings

Do not use

• to sedate a child or make a child sleepy

• if you are now taking a prescription monoamine oxidase inhibitor (MAOI) (certain drugs for

depression, psychiatric, or emotional conditions, or Parkinson's disease), or for 2 weeks after

stopping the MAOI drug. If you do not know if your prescription drug contains an MAOI, ask a

doctor or pharmacist before taking this product

Ask a doctor before use if you have

• trouble urinating due to an enlarged prostate gland

• glaucoma

• a cough that occurs with too much phlegm (mucus)

• a breathing problem or chronic cough that lasts

or as occurs with smoking, asthma, chronic bronchitis

or emphysema

Ask a doctor or pharmacist before use if you are taking sedatives or tranquilizers

When using this product

• Do not use more than directed

• marked drowsiness may occur

• avoid alcoholic drinks

• alcohol, sedatives, and tranquilizers may increase drowsiness

• be careful when driving a motor vehicle or operating machinery

• excitability may occur, especially in children

Stop use and ask a doctor if cough lasts more than 7 days, comes back, or is accompanied by fever,

rash, or persistent headache. These could be signs of a serious condition.

PREGNANCY OR BREAST FEEDING

If pregnant or breast-feeding, ask a health professional before use.

Keep out of reach of children. In case of overdose, get medical help or contact a Poison Control Center right away (1-800-222-1222).

Directions

• SHAKE WELL BEFORE USING

• measure only with dosing cup provided

• keep dosing cup with product • mL = milliliter

• do not take more than 4 doses in any 24-hour period

Age | Dose
Adults and children; 12 years and older | 20 mL every; 6 hours
Children 6 to under 12; years | 10 mL every; 6 hours
Children under 6 years | do not use

Other information

store between 20-25°C (68-77°F)

Inactive ingredients

organic agave syrup, organic blueberry flavor, natural flavors, purified water

Questions? 1-855-436-3921

SHAKE WELL BEFORE EACH USE

DO NOT use if perforated band around the bottle or seal under the cap is disturbed or missing.

Patent Pending | Distributed by: Genexa Inc.

Atlanta, GA 30324 | genexa.com

Made in the USA with globally sourced ingredients

NDC 69676-0088-9

PACKAGE LABEL

Genexa®

MEDICINE MADE CLEAN

Ages 6+

Long Acting

Kids' Nighttime Cough

Chlorpheniramine Maleate - Antihistamine

Dextromethorphan HBr- Cough Suppressant

Relieves Cough up to 8 Hours

Runny Nose

Sneezing

Same active ingredients as leading brands

0% Artificial Additives

Always free of common allergens, artificial preservatives, flavors, & dyes

Organic Blueberry Flavor

4 fl oz (118 mL)